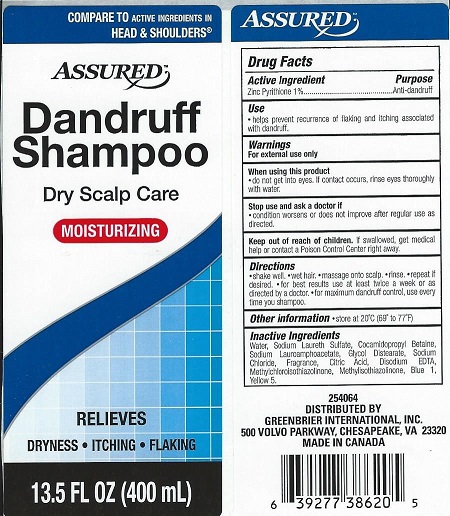 DRUG LABEL: Assured
NDC: 33992-0700 | Form: SHAMPOO
Manufacturer: Greenbrier International Inc.
Category: otc | Type: HUMAN OTC DRUG LABEL
Date: 20210823

ACTIVE INGREDIENTS: PYRITHIONE ZINC 1 g/100 mL
INACTIVE INGREDIENTS: WATER; SODIUM LAURETH SULFATE; COCAMIDOPROPYL BETAINE; SODIUM LAUROAMPHOACETATE; GLYCOL DISTEARATE; SODIUM CHLORIDE; CITRIC ACID MONOHYDRATE; DISODIUM ETHYLENEDIAMINEDIACETATE; METHYLCHLOROISOTHIAZOLINONE; METHYLISOTHIAZOLINONE; FD&C BLUE NO. 1; FD&C YELLOW NO. 5

Assured Dandruff Shampoo

Drug Facts

Active Ingredient

Zinc Pyrithione 1%

Purpose

Anti-dandruff

Use

- helps prevent recurrence of flaking and itching associated with dandruff.

Warnings

For external use only

When using this product

- do not get into eyes. If contact occurs, rinse eyes thoroughly with water.

Stop use and ask a doctor if

- condition worsens or does not improve after regular use as directed.

Keep out of reach of children. If swallowed, get medical help or contact a Poison Control Center right away.

Directions

- shake well.
- wet hair.
- massage into scalp.
- rinse.
- repeat if desired.
- for best results, use at least twice a week or as directed by a doctor.
- for maximum dandruff control, use every time you shampoo.

Other information

- store at 20°C (69° to 77°F)

Inactive Ingredients

Water, Sodium Laureth Sulfate, Cocamidopropyl Betaine, Sodium Lauroamphoacetate, Glycol Distearate, Sodium Chloride, Fragrance, Citric Acid, Disodium EDTA, Methylchloroisothiazolinone, Methylisothiazolinone, Blue 1, Yellow 5.

DISTRIBUTED BY

GREENBRIER INTERNATIONAL, INC.

500 VOLVO PARKWAY

CHESAPEAKE, VA 23320

MADE IN CANADA

PACKAGE LABEL

ASSURED™

Dandruff Shampoo

Dry Scalp Care

MOISTURIZING

RELIEVES

DRYNESS • ITCHING • FLAKING

13.5 FL OZ (400 mL)